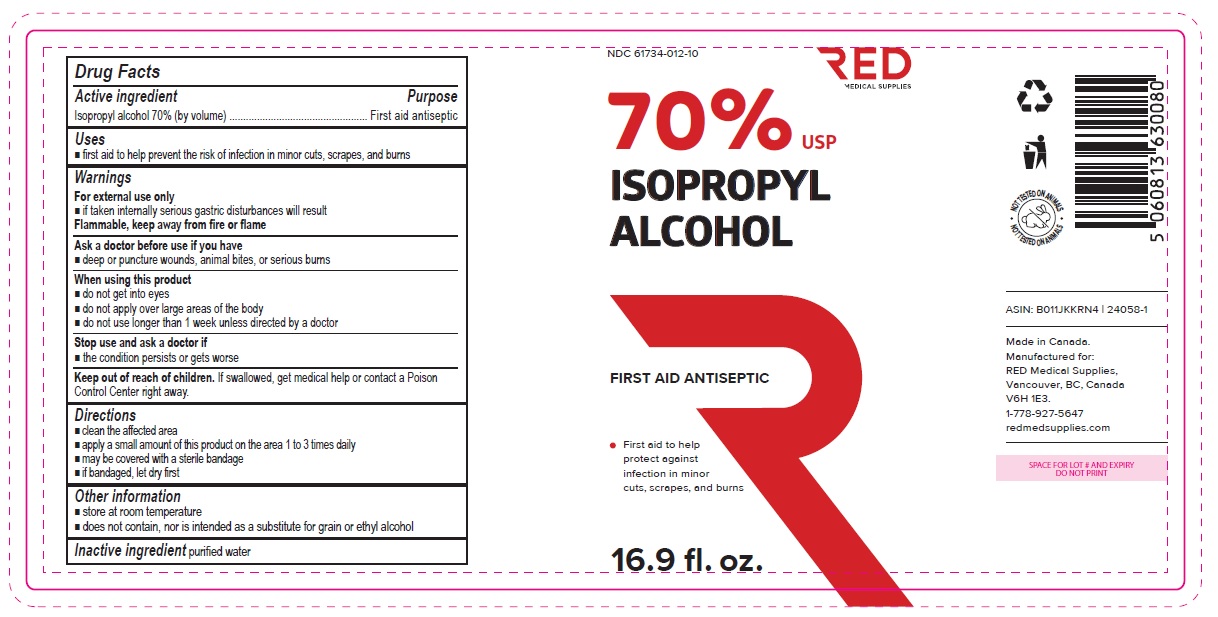 DRUG LABEL: Isopropyl Rubbing Alcohol 70
NDC: 61734-012 | Form: SOLUTION
Manufacturer: Delon Laboratories (1990) Ltd.
Category: otc | Type: HUMAN OTC DRUG LABEL
Date: 20251016

ACTIVE INGREDIENTS: ISOPROPYL ALCOHOL 70 mL/100 mL
INACTIVE INGREDIENTS: WATER

Isopropyl Alcohol 70%

Active ingredient

Isopropyl alcohol 70% (by volume)

Purpose

First aid antiseptic

Uses

- first aid to help prevent the risk of infection in minor cuts, scrapes, and burns

Warnings

For external use only

- if taken internally serious gastric disturbances will result

Flammable, keep away from fire or flame

Ask a doctor before use if you have

- deep or puncture wounds, animal bites, or serious burns

When using this product

- do not get into eyes
- do not apply over large areas of the body
- do not use longer than 1 week unless directed by a doctor

Stop use and ask a doctor if

- the condition persists or gets worse

Keep out of reach of children. If swallowed, get medical help or contact a Poison Control Center right away.

Directions

- clean the affected area
- may be covered with a sterile bandage
- if bandaged, let dry first

DOSAGE AND ADMINISTRATION

- apply a small amount of this product on the area 1 to 3 times daily

Other information

- store at room temperature
- does not contain, nor is intended as a substitute for grain or ethyl alcohol

Inactive ingredient

purified water